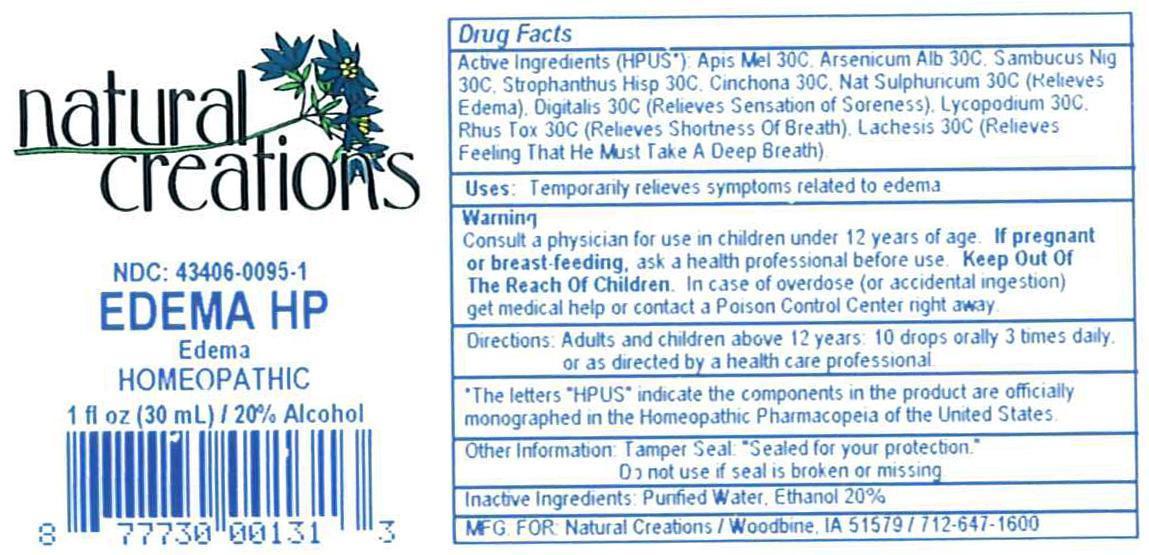 DRUG LABEL: EDEMA HP
NDC: 43406-0095 | Form: LIQUID
Manufacturer: Natural Creations, Inc.
Category: homeopathic | Type: HUMAN OTC DRUG LABEL
Date: 20121031

ACTIVE INGREDIENTS: APIS MELLIFERA 30 [hp_C]/1 mL; ARSENIC TRIOXIDE 30 [hp_C]/1 mL; CINCHONA OFFICINALIS BARK 30 [hp_C]/1 mL; DIGITALIS 30 [hp_C]/1 mL; LACHESIS MUTA VENOM 30 [hp_C]/1 mL; LYCOPODIUM CLAVATUM SPORE 30 [hp_C]/1 mL; SODIUM SULFATE 30 [hp_C]/1 mL; TOXICODENDRON PUBESCENS LEAF 30 [hp_C]/1 mL; SAMBUCUS NIGRA FLOWERING TOP 30 [hp_C]/1 mL; STROPHANTHUS HISPIDUS SEED 30 [hp_C]/1 mL
INACTIVE INGREDIENTS: WATER; ALCOHOL

EDEMA HP

ACTIVE INGREDIENT

ACTIVE INGREDIENTS (HPUS*): Apis Mellifica 30C, Arsenicum Album 30C, Cinchona Officinalis 30C, Digitalis Purpurea 30C, Lachesis Mutus 30C, Lycopodium Clavatum 30C, Natrum Sulphuricum 30C, Rhus Toxicodendron 30C, Sambucus Nigra 30C, Strophanthus Hispidus 30C

INDICATIONS AND USAGE

USES: Temporarily relieves sensation of soreness, shortness of breath, feeling that deep breaths must be taken, &/or symptoms related to edema.

WARNING:

Consult a physician for use in children under 12 years of age. IF PREGNANT OR BREAST-FEEDING, ask a health care professional before use. KEEP OUT OF THE REACH OF CHILDREN. In case of overdose (or accidental ingestion) get medical help or contact a Poison Control Center right away.

DOSAGE AND ADMINISTRATION

DIRECTIONS: Adults and children above 12 years: 10 drops orally 3 times daily, or as directed by a health care professional.

OTHER INFORMATION: Tamper Seal: "Sealed for your protection."

Do not use if seal is broken or missing.

REFERENCES

*The letters "HPUS" indicate the components in the product are officially monographed in the Homeopathic Pharmacopeia of the United States.

INACTIVE INGREDIENTS: Purified Water, USP Ethanol Alcohol 20%

QUESTIONS AND COMMENTS?

MFGO FOR: Natural Creations / Woodbine, IA / 51579 712.647.1600

LOT:

PURPOSE

USES: Temporarily relieves sensation of soreness, shortness of breath, feeling that deep breaths must be taken, &/or symptoms related to edema.

KEEP OUT OF REACH OF CHILDREN

KEEP OUT OF THE REACH OF CHILDREN. In case of overdose (or accidental ingestion) get medical help or contact a Poison Control Center.

PACKAGE LABEL

NDC: 43406-0095-1

EDEMA HP

Edema

HOMEOPATHIC

1 fl oz (30 mL) / 20% Alcohol

UPC: 877730001313